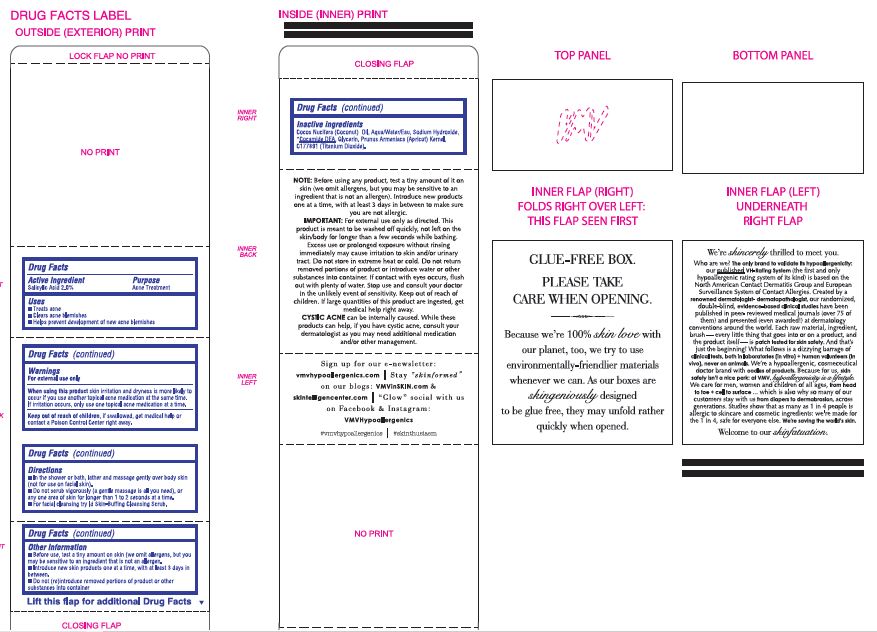 DRUG LABEL: ID CLARIFYING BODY
NDC: 69774-554 | Form: SOAP
Manufacturer: SKIN SCIENCES LABORATORY INC.
Category: otc | Type: HUMAN OTC DRUG LABEL
Date: 20170425

ACTIVE INGREDIENTS: SALICYLIC ACID 1.35 g/135 g
INACTIVE INGREDIENTS: WATER; SODIUM HYDROXIDE; COCAMIDE; GLYCERIN; TITANIUM DIOXIDE

ID CLARIFYING BODY SOAP

Active Ingredient
Salicylic Acid 2.0%

Purpose
Acne Treatment

Purpose
Acne Treatment

Uses

• Treats acne
• Clears acne blemishes
• Helps prevent development of new acne blemishes

Warnings
For external use only

When using this product skin irritation and dryness is more likely to occur if you use another topical acne medication at the same time. If irritation occurs, only use one topical acne medication at a time.

Keep out of reach of children, if swallowed, get medical help or contact a Poison Control Center right away.

Directions

• In the shower or bath, lather and massage gently over body skin (not for use on facial skin).
• Do not scrub vigorously {a gentle massage is all you need), or any one area of skin for longer than 1 to 2 seconds at a time.
• For facial cleansing try Id Skin-Buffing Cleansing Scrub.

OTHER SAFETY INFORMATION

• Before use, test a tiny amount on skin (we omit allergens, but you may be sensitive to an ingredient that is not an allergen.
• Introduce new skin products one at a time, with at least 3 days in between.
• Do not (re)introduce removed portions of product or other substances into container

NOTE: Before using any product, test a tiny amount of it on skin (we omit allergens, but you may be sensitive to an ingredient that is not an allergen). Introduce new products one at a time, with at least 3 days in between to make sure you are not allergic.
IMPORTANT: For external use only as directed. This product is meant to be washed off quickly, not left on the skin/body for longer than a few seconds while bathing. Excess use or prolonged exposure without rinsing immediately may cause irritation to skin and/or urinary tract. Do not store in extreme heat or cold. Do not return removed portions of product or introduce water or other substances into container. If contact with eyes occurs, flush out with plenty of water. Stop use and consult your doctor in the unlikely event of sensitivity. Keep out of reach of children. If large quantities of this product are ingested, get medical help right away.

CYSTIC ACNE can be internally caused. While these products can help, if you have cystic acne, consult your dermatologist as you may need additional medication and/or other management.

Inactive ingredients
Cocos Nucifera (Coconut) Oil, Aqua/Water/Eau, Sodium Hydroxide, Cocamlde DEA, Glycerin, Prunus Armeniaca (Apricot) Kernel, C177891 (Titanium Dioxide).

PACKAGE LABEL

VMV HYPOALLERGENICS
validated hypoallergenic.
randomized, blinded, published &
awarded clinical studies. since 1979

id

CLARIFYING BODY SOAP

exfoliating body cleanser

salicylic acid + apricot kernels

Validated Hypoallergenic: VH -108/109

sans common allergens: NACDG + ESSCA

100% All-Types-Of-Fragrance-Dye-Phthalate-Paraben-

Preservative-SLS + SLES-Free. Usage + Patch-Tested

(in vivo + in vitro). Non-Drying. Non-Comedogenic.

For All Skin Types. For Men + Women, 18+.

135 g (4.76 Oz.) - 135 g